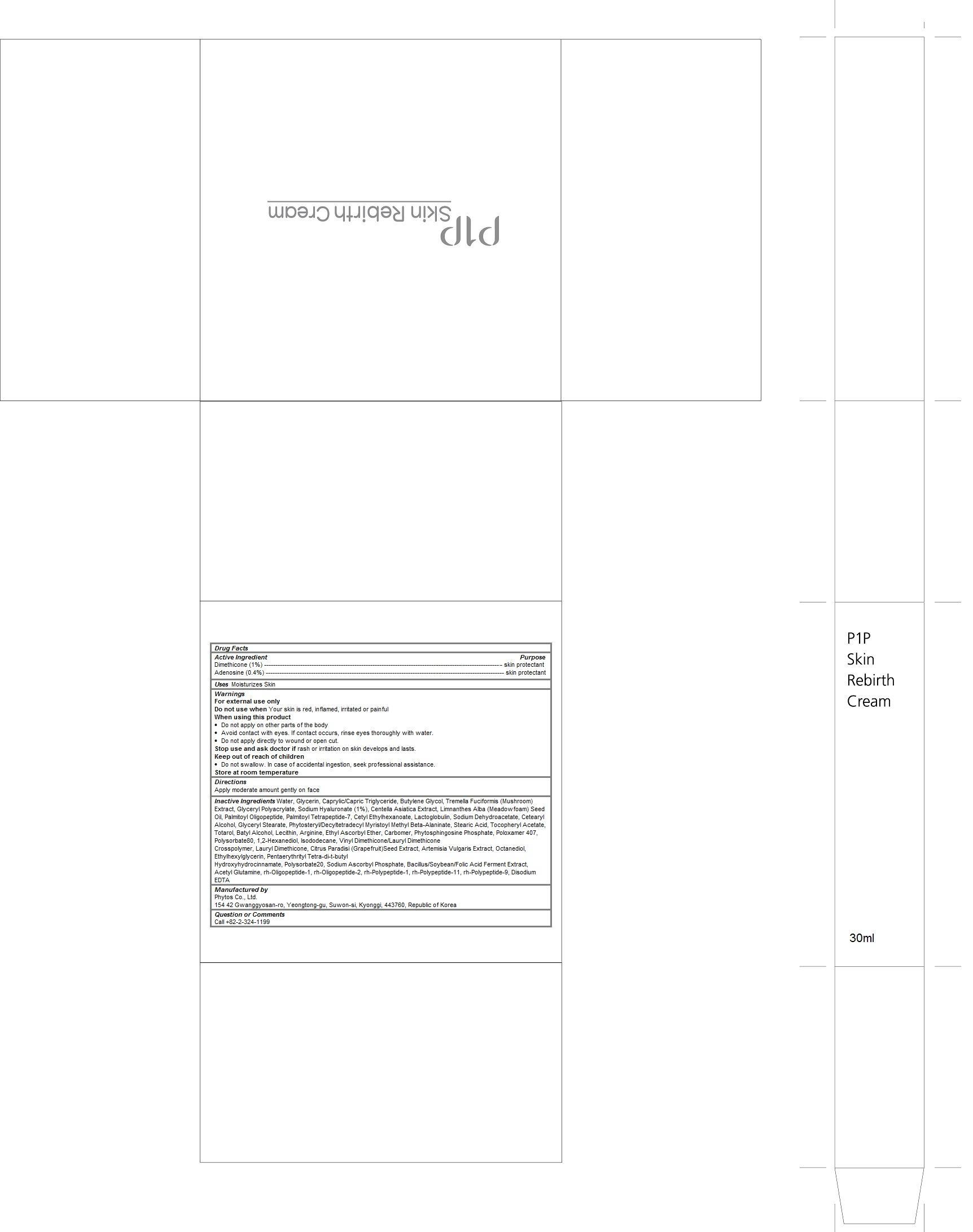 DRUG LABEL: P1P Skin Rebirth Cream
NDC: 69579-103 | Form: CREAM
Manufacturer: Phytos Co., Ltd.
Category: otc | Type: HUMAN OTC DRUG LABEL
Date: 20150126

ACTIVE INGREDIENTS: dimethicone 0.01 1/30 mL; adenosine 0.004 1/30 mL
INACTIVE INGREDIENTS: water; glycerin; MEDIUM-CHAIN TRIGLYCERIDES; BUTYLENE GLYCOL; TREMELLA FUCIFORMIS WHOLE; HYALURONATE SODIUM; CENTELLA ASIATICA; MEADOWFOAM SEED OIL; PALMITOYL OLIGOPEPTIDE; PALMITOYL TETRAPEPTIDE-7; cetyl ethylhexanoate; SODIUM DEHYDROACETATE; CETOSTEARYL ALCOHOL; GLYCERYL MONOSTEARATE; stearic acid; .ALPHA.-TOCOPHEROL ACETATE; totarol; BATILOL; EGG PHOSPHOLIPIDS; ARGININE; poloxamer 407; polysorbate 80; 1,2-HEXANEDIOL; isododecane; DIMETHICONE/VINYL DIMETHICONE CROSSPOLYMER (HARD PARTICLE); LAURYL TRISILOXANE; CITRUS PARADISI SEED; ARTEMISIA VULGARIS ROOT; octanediol; ethylhexylglycerin; PENTAERYTHRITOL TETRAKIS(3-(3,5-DI-TERT-BUTYL-4-HYDROXYPHENYL)PROPIONATE); polysorbate 20; SODIUM ASCORBYL PHOSPHATE; ACEGLUTAMIDE; NEPIDERMIN; MECASERMIN; BASIC FIBROBLAST GROWTH FACTOR (HUMAN); FIBROBLAST GROWTH FACTOR-1; EDETATE DISODIUM

P1P Skin Rebirth Cream